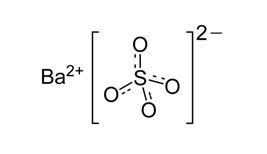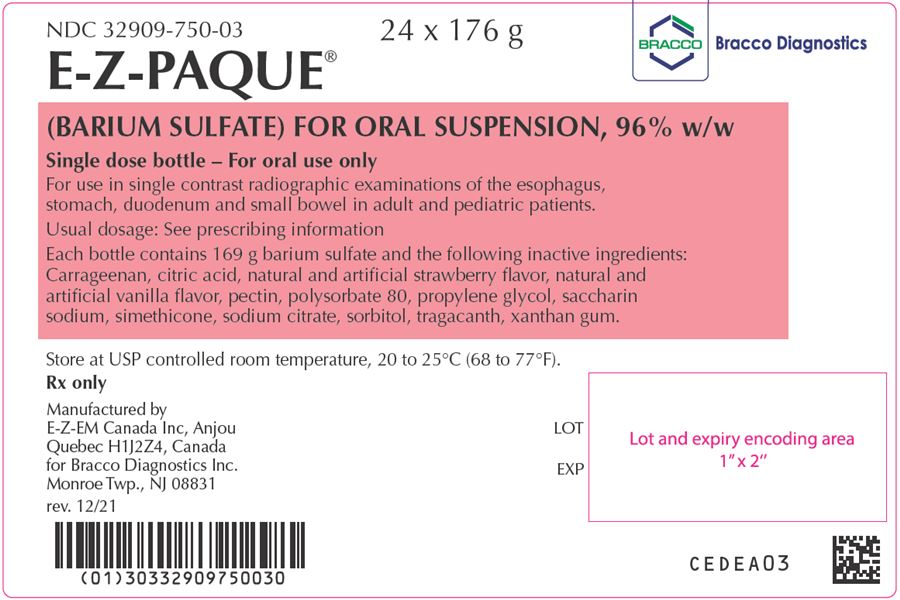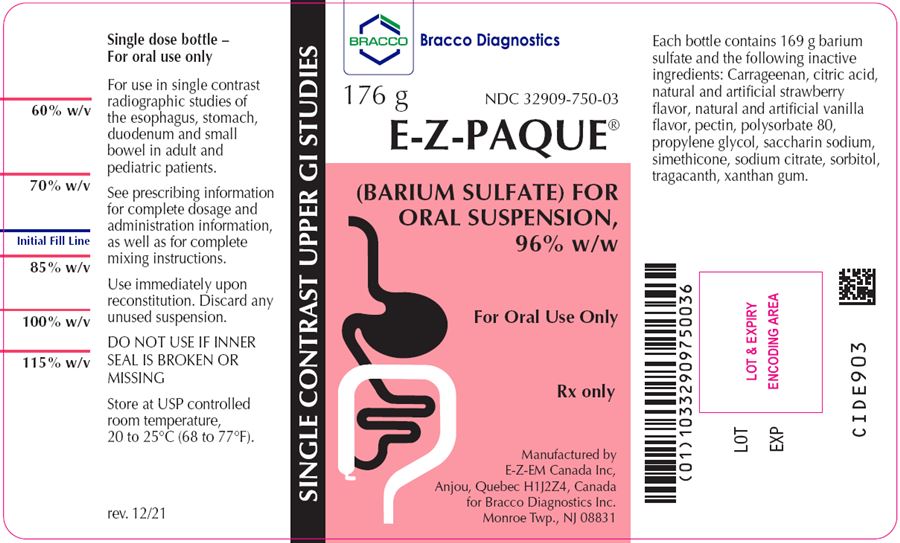 DRUG LABEL: E-Z-Paque
NDC: 32909-750 | Form: POWDER, FOR SUSPENSION
Manufacturer: E-Z-EM Canada Inc
Category: prescription | Type: HUMAN PRESCRIPTION DRUG LABEL
Date: 20221107

ACTIVE INGREDIENTS: Barium Sulfate 960 mg/1 g
INACTIVE INGREDIENTS: anhydrous citric acid; dimethicone 1000; pectin; polysorbate 80; propylene glycol; silicon dioxide; carrageenan sodium; sorbitol; tragacanth; xanthan gum; trisodium citrate dihydrate; saccharin sodium

HIGHLIGHTS OF PRESCRIBING INFORMATION

These highlights do not include all the information needed to use E-Z-PAQUE safely and effectively. See full prescribing information for E-Z-PAQUE.
E-Z-PAQUE (barium sulfate) for oral suspension
Initial U.S. Approval: 2016

1 INDICATIONS AND USAGE

E-Z-PAQUE is a radiographic contrast agent indicated for use in single contrast radiographic examinations of the esophagus, stomach, duodenum and small bowel to visualize the gastrointestinal (GI) tract in adult and pediatric patients (1)

2 DOSAGE AND ADMINISTRATION

- Adults: Recommended reconstituted oral dose is between 150 – 750 mL (2.1)
- Pediatric patients: adjust reconstituted dose based on relative GI volume (2.1)
- Must reconstitute supplied powder with water prior to use. See Full Prescribing Information for reconstitution instructions (2.2)

3 DOSAGE FORMS AND STRENGTHS

- For oral suspension: 169 grams of barium sulfate (96% w/w) in a single-dose bottle for reconstitution (3)

4 CONTRAINDICATIONS

- Known or suspected perforation of the GI tract (4)
- Known obstruction of the GI tract (4)
- Conditions associated to high risk of GI aspiration (4)
- Conditions associated to high risk of GI perforation (4)
- Known hypersensitivity to barium sulfate or any of the excipients of E-Z-PAQUE (4)

5 WARNINGS AND PRECAUTIONS

- Hypersensitivity reactions: Emergency equipment and trained personnel should be immediately available (5.1)
- Intra-abdominal barium leakage: May occur in conditions such as GI fistula, ulcer, inflammatory bowel disease, appendicitis or diverticulitis, severe stenosis or obstructing lesions of the GI tract (5.2)
- Delayed GI transit and obstruction: Patients should maintain adequate hydration in days following a barium sulfate procedure to avoid obstruction or impaction caused by baroliths (5.3)
- Aspiration pneumonitis: Patients with history of food aspiration or with swallowing disorders are at increased risk. (5.4)

6 ADVERSE REACTIONS

Common adverse reactions include nausea, vomiting, diarrhea and abdominal cramping (6)

To report SUSPECTED ADVERSE REACTIONS, contact Bracco Diagnostics Inc at 1-800-257-5181 or FDA at 1-800-FDA-1088 or www.fda.gov/medwatch

FULL PRESCRIBING INFORMATION

1 INDICATIONS AND USAGE

E-Z-PAQUE is indicated for use in single contrast radiographic examinations of the esophagus, stomach, duodenum and small bowel to visualize the gastrointestinal tract (GI) in adult and pediatric patients.

2 DOSAGE AND ADMINISTRATION

2.1 Recommended Dosage

The optimal oral dose of E-Z-PAQUE will vary depending on the size and anatomy of the patient and the procedure being performed. The recommended oral dose of reconstituted E-Z-PAQUE:

- Adults: 150 to 750 mL, 169 to 450 g barium sulfate, depending on the reconstituted concentration [see Dosage and Administration (2.2)].
  - Volumes closer to 150 mL are recommended for examination of the esophagus and stomach.
  - Volumes up to 750 mL are recommended for examination of the small bowel.
- Pediatric Patients: Adjust dose of reconstituted E-Z-PAQUE based on GI volume.
  - For examinations of the upper GI tract, administer a volume sufficient to fully distend the esophagus or stomach.
  - For small bowel examinations:
    - Age birth to less than 2 years: 30 mL to 75 mL.
    - Age 2 years to less than 17 years: 75 mL to 480 mL.

2.2 Instructions for Reconstitution

The reconstituted concentration will vary, depending on the procedure being performed.

- A barium suspension up to 115% w/v is recommended for examinations of the esophagus and upper GI
- A barium suspension of 60% w/v is recommended for examinations of the small bowel.

Reconstitute the E-Z-PAQUE prior to administration according to the following instructions:

- Tap bottle on a hard surface (right side up) several times to compact the product in the bottle.
- Add water to the blue line marked ‘Initial Fill Line’ on the bottle.
- Replace cap securely on the bottle.
- Invert bottle and tap with fingers to mix contrast into the water.
- Shake vigorously for 30 seconds; wait 5 minutes.
- Add more water as needed to achieve the desired % w/v concentration using the fill lines marked on the bottle. Then, re-shake vigorously for 30 seconds.
- To use with straw, remove adhesive label on top of cap.
- Remove cap and use straw to push out cap liner; replace cap.

2.3 Administration Instructions

- Use immediately after reconstitution.
- Ensure patients have nothing by mouth for the following time period prior to the examination:
  - Neonates and infants < 3 months 2 hours
  - Infants 3-12 months 3 hours
  - > 12 months of age 4 hours
- Discard any unused suspension.
- Encourage patients to maintain hydration following the barium sulfate procedure.

3 DOSAGE FORMS AND STRENGTHS

For oral suspension: 169 g of barium sulfate supplied as a fine, white to lightly colored powder (96 % w/w) in a single-dose HDPE plastic bottle for reconstitution. The suspension can be reconstituted to a desired strength of 60, 70, 85, 100, or 115% w/v when prepared according to the corresponding fill line on the bottle. The reconstituted solution should be opaque, white to lightly-colored and free from particles.

4 CONTRAINDICATIONS

E-Z-PAQUE is contraindicated in patients with the following conditions:

- Known or suspected perforation of the GI tract
- Known obstruction of the GI tract
- High risk of GI perforation such as those with a recent prior GI perforation, acute GI hemorrhage or ischemia, toxic megacolon, severe ileus, post GI surgery or biopsy, acute GI injury or burn, or recent radiotherapy to the pelvis
- High risk of aspiration such as those with prior aspiration, tracheo-esophageal fistula, or obtundation
- With known severe hypersensitivity to barium sulfate or any of the excipients of E-Z-PAQUE

5 WARNINGS AND PRECAUTIONS

5.1 Hypersensitivity Reactions

Barium sulfate preparations contain a number of excipients, including natural and artificial flavors and may induce serious hypersensitivity reactions. The manifestations include hypotension, bronchospasm and other respiratory impairments, dermal reactions including rashes, urticaria, and itching. A history of bronchial asthma, atopy, or a previous reaction to a contrast agent may increase the risk for hypersensitivity reactions. Emergency equipment and trained personnel should be immediately available for treatment of a hypersensitivity reaction.

5.2 Intra-abdominal Barium Leakage

The use of E-Z-PAQUE is contraindicated in patients at high risk of perforation of the GI tract [see Contraindications (4)]. Administration of E-Z-PAQUE may result in leakage of barium from the GI tract in the presence of conditions such as carcinomas, GI fistula, inflammatory bowel disease, gastric or duodenal ulcer, appendicitis, diverticulitis, and in patients with a severe stenosis at any level of the GI tract, especially distal to the stomach. Barium leakage has been associated with peritonitis and granuloma formation.

5.3 Delayed Gastrointestinal Transit and Obstruction

Orally administered barium sulfate may accumulate proximal to a constricting lesion of the colon, causing obstruction or impaction with development of baroliths (inspissated barium associated with feces) and may cause abdominal pain, appendicitis, bowel obstruction, or rarely perforation. Patients with the following conditions are at higher risk for developing obstruction or baroliths: severe stenosis at any level of the GI tract, impaired GI motility, electrolyte imbalance, dehydration, on a low residue diet, on medications that delay GI motility, constipation, cystic fibrosis, Hirschsprung disease, and the elderly [see Use in Specific Populations (8.4, 8.5)]. To reduce the risk of delayed GI transit and obstruction, patients should maintain adequate hydration during and in the days following a barium sulfate procedure. Consider the administration of laxatives.

5.4 Aspiration Pneumonitis

The use of E-Z-PAQUE is contraindicated in patients at high risk of aspiration [see Contraindications (4)]. Oral administration of barium is associated with aspiration pneumonitis, especially in patients with a history of food aspiration or with compromised swallowing mechanism. Vomiting following oral administration of barium sulfate may lead to aspiration pneumonitis. In patients at risk for aspiration, begin the procedure with a small ingested volume of E-Z-PAQUE. Discontinue administration of E-Z-PAQUE immediately if aspiration is suspected.

5.5 Systemic Embolization

Barium sulfate products may occasionally intravasate into the venous drainage of the large bowel and enter the circulation as a "barium embolus" leading to potentially fatal complications which include systemic and pulmonary embolism, disseminated intravascular coagulation, septicemia and prolonged severe hypotension. Although this complication is exceedingly uncommon after oral administration of a barium sulfate suspension, monitor patients for potential intravasation when administering barium sulfate.

5.6 Risk with Hereditary Fructose Intolerance

E-Z-PAQUE contains sorbitol which may cause severe symptoms if ingested by patients with hereditary fructose intolerance. Severe symptoms may include the following: vomiting, hypoglycemia, jaundice, hemorrhage, hepatomegaly, hyperuricemia, and kidney failure. Before administration of E-Z-PAQUE assess patients for a history of hereditary fructose intolerance and avoid use in these patients.

6 ADVERSE REACTIONS

The following adverse reactions have been identified from spontaneous reporting or clinical studies of barium sulfate administered orally. Because the reactions are reported voluntarily from a population of uncertain size, it is not always possible to reliably estimate their frequency or to establish a causal relationship to drug exposure

- Nausea, vomiting, diarrhea and abdominal cramping
- Serious adverse reactions and fatalities include aspiration pneumonitis, barium sulfate impaction, intestinal perforation with consequent peritonitis and granuloma formation, vasovagal and syncopal episodes

8 USE IN SPECIFIC POPULATIONS

8.1 Pregnancy

Risk Summary

E-Z-PAQUE is not absorbed systemically following oral administration, and maternal use is not expected to result in fetal exposure to the drug [see Clinical Pharmacology (12.3)].

8.2 Lactation

Risk Summary

E-Z-PAQUE is not absorbed systemically by the mother following oral administration, and breastfeeding is not expected to result in exposure of the infant to E-Z-PAQUE [see Clinical Pharmacology (12.3)].

8.4 Pediatric Use

The efficacy of E-Z-PAQUE in pediatric patients from birth to less than 17 years of age is based on successful opacification of the esophagus, stomach, duodenum and small bowel during radiologic examinations [see Clinical Pharmacology (12.1)]. Safety and dosing recommendations in pediatric patients are based on clinical experience [see Dosage and Administration (2.1)].

E-Z-PAQUE is contraindicated in pediatric patients with tracheo-esophageal fistula [see Contraindications (4)]. Pediatric patients with a history of asthma or food allergies may be at increased risk for development of hypersensitivity reactions [see Warnings and Precautions (5.1)]. Pediatric patients with cystic fibrosis or Hirschsprung disease should be monitored for bowel obstruction after use [see Warnings and Precautions (5.3)]. Pediatric patients with hereditary fructose intolerance may develop severe symptoms with administration of E-Z-Paque; assess for this risk and avoid use in patients with hereditary fructose intolerance [see Warnings and Precautions (5.6)].

8.5 Geriatric Use

Clinical studies of E-Z-PAQUE did not include sufficient numbers of subjects aged 65 and over to determine whether they respond differently from younger subjects. Other reported clinical experience has not identified differences in responses between the elderly and younger patients. In general, dose selection for an elderly patient should be cautious, usually starting at the low end of the dosing range, reflecting the greater frequency of decreased hepatic, renal, or cardiac function, and of concomitant disease or other drug therapy.

11 DESCRIPTION

E-Z-PAQUE (barium sulfate) is a radiographic contrast agent that is supplied as a fine, white to lightly colored powder for suspension (96 % w/w) for oral administration. The active ingredient barium sulfate is designated chemically as BaSO4 with a molecular weight of 233.4 g/mol, a density of 4.5 g/cm^3, and the following chemical structure:

E-Z-PAQUE contains excipients including: carrageenan, citric acid, natural and artificial natural and artificial strawberry flavor, natural and artificial vanilla flavor, pectin, polysorbate 80, propylene glycol, saccharin sodium, simethicone, sodium citrate, sorbitol, tragacanth and xanthan gum.

12 CLINICAL PHARMACOLOGY

12.1 Mechanism of Action

Due to its high atomic number, barium (the active ingredient in E-Z-PAQUE) is opaque to x-rays and therefore acts as a positive contrast agent for radiographic studies.

12.3 Pharmacokinetics

Under physiological conditions, barium sulfate passes through the GI tract in an unchanged form and is absorbed only in pharmacologically insignificant amounts.

13 NONCLINICAL TOXICOLOGY

13.1 Carcinogenesis, Mutagenesis, Impairment of Fertility

No animal studies have been performed to evaluate the carcinogenic potential of barium sulfate or potential effects on fertility.

16 HOW SUPPLIED/STORAGE AND HANDLING

How Supplied

E-Z-PAQUE (barium sulfate) is supplied as a fine white to lightly colored powder (96 % w/w) in a single dose HDPE plastic bottle containing 169 g of barium sulfate.

Provided as: 24 bottles per pack (NDC 32909-750-03)

Storage and Handling

Store at USP controlled room temperature 20 to 25°C (68 to 77° F).

17 PATIENT COUNSELING INFORMATION

After administration advise patients to:

- Maintain adequate hydration
- Seek medical attention for worsening of constipation or slow gastrointestinal passage
- Seek medical attention for any delayed onset of hypersensitivity: rash, urticaria, or respiratory difficulty

Manufactured by:
EZEM Canada Inc
Anjou (Quebec) Canada H1J 2Z4
for:
Bracco Diagnostics Inc.
Monroe Township, NJ 08831

CLDEB02

Revised December 2021

PACKAGE LABEL

E-Z-Paque
NDC: 32909-750-03
Barium Sulfate For Suspension

Labels